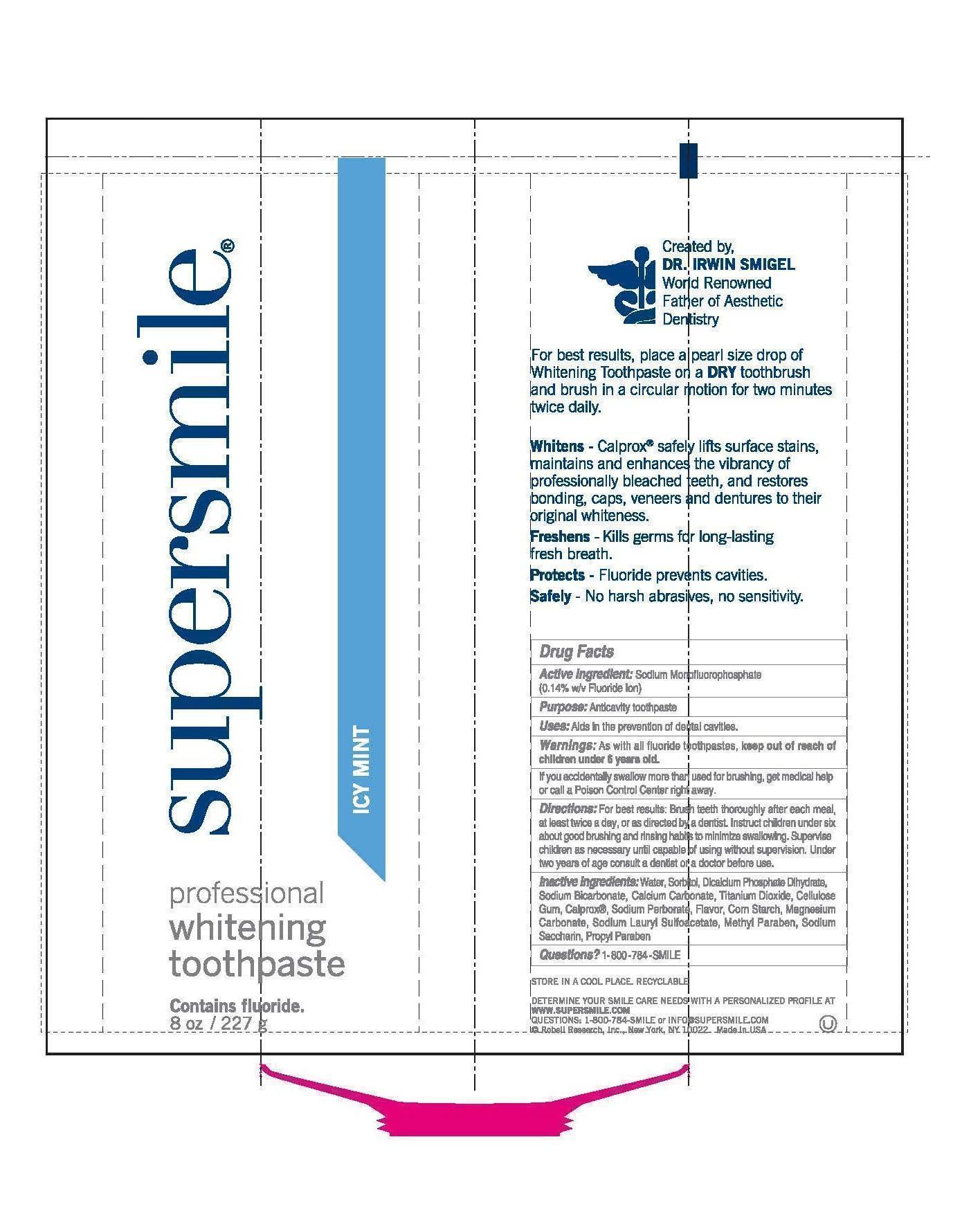 DRUG LABEL: SuperSmile Professional
NDC: 53567-0101 | Form: PASTE, DENTIFRICE
Manufacturer: ROBELL RESEARCH, INC.
Category: otc | Type: HUMAN OTC DRUG LABEL
Date: 20121003

ACTIVE INGREDIENTS: SODIUM MONOFLUOROPHOSPHATE 0.76 g/100 g
INACTIVE INGREDIENTS: WATER; CALCIUM PEROXIDE; SODIUM PERBORATE; SODIUM BICARBONATE; CALCIUM PHOSPHATE, DIBASIC, ANHYDROUS; CALCIUM CARBONATE; MAGNESIUM CARBONATE; STARCH, CORN; SACCHARIN; METHYLPARABEN; PROPYLPARABEN; TITANIUM DIOXIDE; CARBOXYMETHYLCELLULOSE SODIUM; SODIUM LAURYL SULFOACETATE

Drug Facts

Active Ingredient:

Sodium Monofluorophosphate (0.14% w/v Fluoride Ion)

Purpose:

Anticavity toothpaste

Uses:

Aids in the prevention of dental cavities.

Warnings:

As with all fluoride toothpastes,

children under 6 years old.

Directions:

For best results: Brush teeth thoroughly after each meal, at least twice a day, or as directed by a dentist.

Directions:

Instruct children under six about good brushing and rinsing habits to minimize swallowing. Supervise children as necessary until capable of using without supervision. Under two years of age consult a dentist or a doctor before use.

Inactive Ingredients:

Water, Sorbitol, Dicalcium Phosphate Dihydrate, Sodium Bicarbonate, Calcium Carbonate, Titanium Dioxide, Cellulose Gum, Calprox®, Sodium Perborate, Flavor, Corn Starch, Magnesium Carbonate, Sodium Lauryl Sulfoacetate, Methyl Paraben, Sodium Saccharin, Propyl Paraben

Questions:

1-800 -784 -SMILE